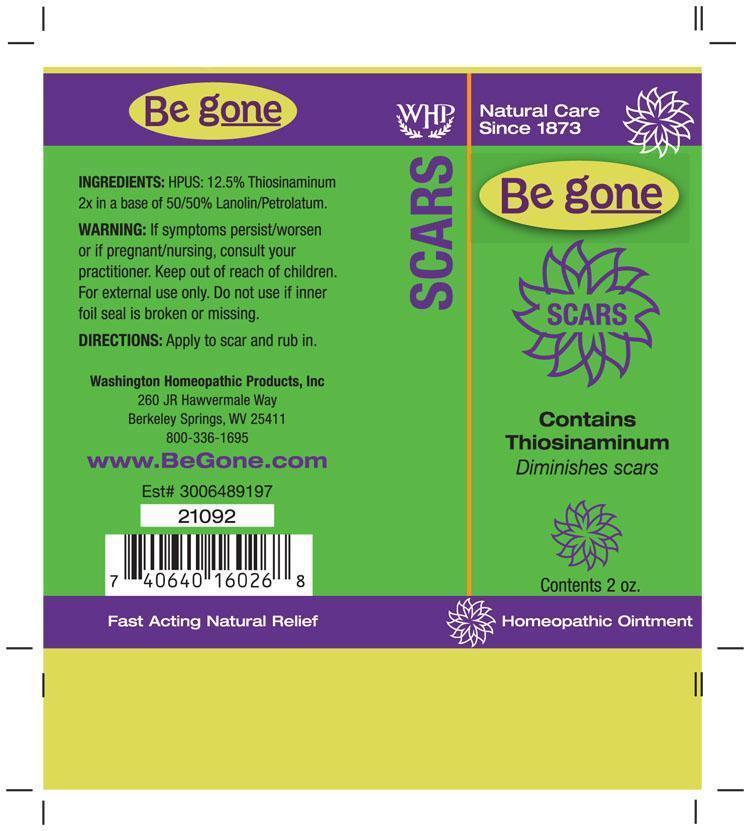 DRUG LABEL: Be gone Scars
NDC: 68428-721 | Form: OINTMENT
Manufacturer: Washington Homeopathic Products
Category: homeopathic | Type: HUMAN OTC DRUG LABEL
Date: 20191223

ACTIVE INGREDIENTS: ALLYLTHIOUREA 2 [hp_X]/56 g
INACTIVE INGREDIENTS: PETROLATUM; LANOLIN

DRUG FACTS

ACTIVE INGREDIENTS

THIOSINAMINUM 2X

USES

To diminish scars.

KEEP OUT OF REACH OF CHILDREN

Keep this and all medicines out of reach of children.

INDICATIONS

THIOSINAMINUM Scarring

STOP USE AND ASK DOCTOR

For external use only. If symptoms persist/worsen or if pregnant/nursing, consult your practitioner. Do not use if inner foil seal is broken or missing.

DIRECTIONS

Apply to scar and rub in.

INACTIVE INGREDIENTS

50% Lanolin

50% Petrolatum

PRINCIPAL DISPLAY PANEL

Be gone Scars tube